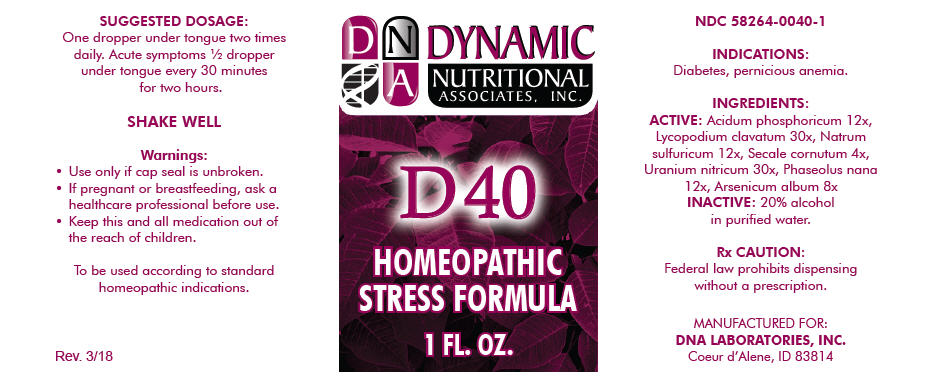 DRUG LABEL: D-40
NDC: 58264-0040 | Form: SOLUTION
Manufacturer: DNA Labs, Inc.
Category: homeopathic | Type: HUMAN OTC DRUG LABEL
Date: 20250113

ACTIVE INGREDIENTS: PHOSPHORIC ACID 12 [hp_X]/1 mL; LYCOPODIUM CLAVATUM SPORE 30 [hp_X]/1 mL; SODIUM SULFATE 12 [hp_X]/1 mL; CLAVICEPS PURPUREA SCLEROTIUM 4 [hp_X]/1 mL; URANYL NITRATE HEXAHYDRATE 30 [hp_X]/1 mL; PHASEOLUS VULGARIS WHOLE 12 [hp_X]/1 mL; ARSENIC TRIOXIDE 8 [hp_X]/1 mL
INACTIVE INGREDIENTS: ALCOHOL; WATER

D-40

NDC 58264-0040-1

INDICATIONS

PURPOSE

Diabetes, pernicious anemia.

INGREDIENTS

ACTIVE

Acidum phosphoricum 12x, Lycopodium clavatum 30x, Natrum sulfuricum 12x, Secale cornutum 4x, Uranium nitricum 30x, Phaseolus nana 12x, Arsenicum album 8x

INACTIVE

20% alcohol in purified water.

Rx CAUTION

Federal law prohibits dispensing without a prescription.

SUGGESTED DOSAGE

One dropper under tongue two times daily. Acute symptoms ½ dropper under tongue every 30 minutes for two hours.

STORAGE AND HANDLING

SHAKE WELL

Warnings

- Use only if cap seal is unbroken.

PREGNANCY OR BREAST FEEDING

- If pregnant or breastfeeding, ask a healthcare professional before use.

KEEP OUT OF REACH OF CHILDREN

- Keep this and all medication out of the reach of children.

To be used according to standard homeopathic indications.

PRINCIPAL DISPLAY PANEL - 1 FL. OZ. Bottle Label

DYNAMIC
NUTRITIONAL
ASSOCIATES, INC.

D 40

HOMEOPATHIC
STRESS FORMULA

1 FL. OZ.